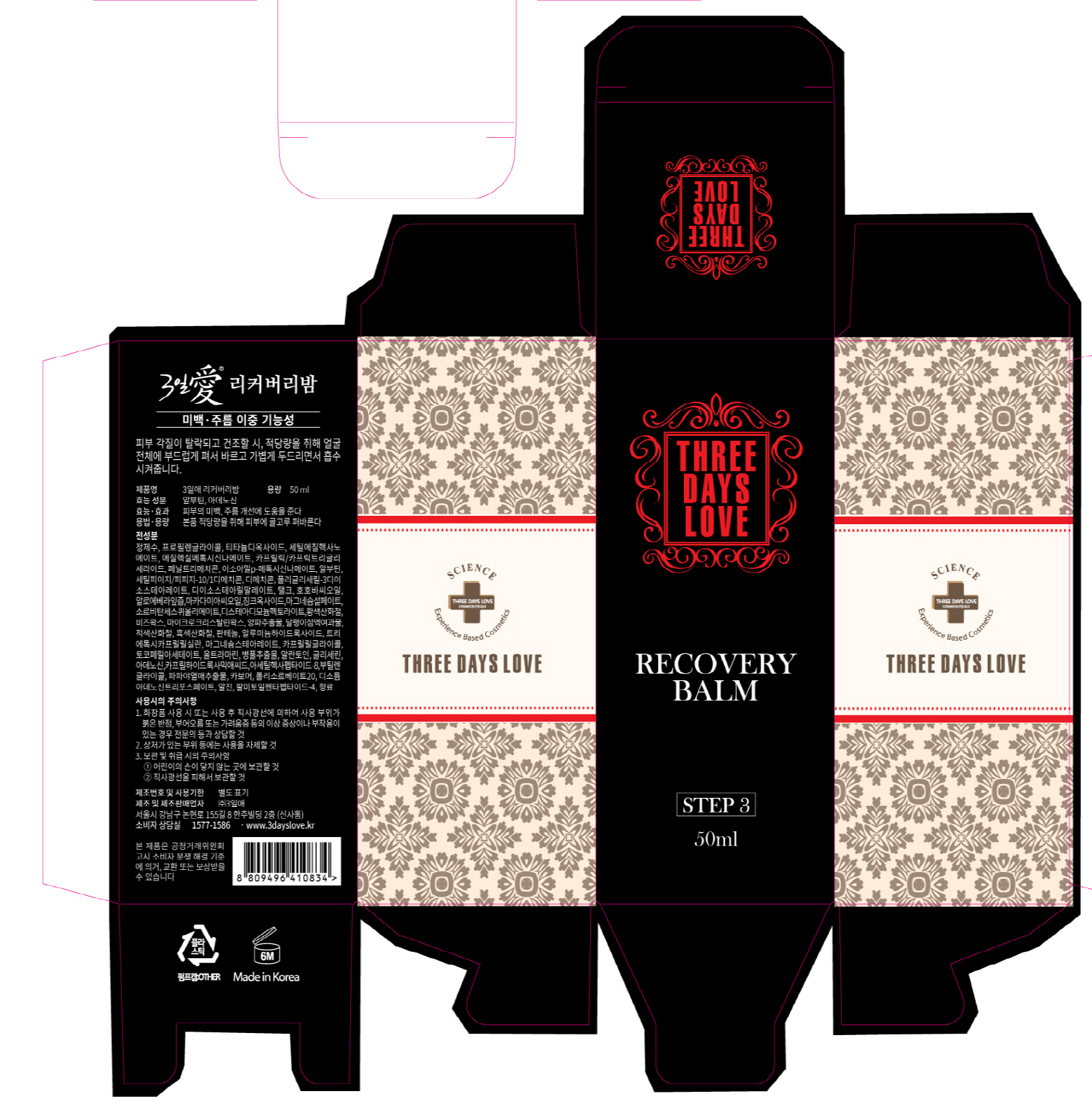 DRUG LABEL: Recovery Balm
NDC: 72368-0003 | Form: LIQUID
Manufacturer: Threedayslove Co., Ltd.
Category: otc | Type: HUMAN OTC DRUG LABEL
Date: 20200103

ACTIVE INGREDIENTS: ARBUTIN 2 g/100 mL; ADENOSINE 0.04 g/100 mL
INACTIVE INGREDIENTS: WATER; BUTYLENE GLYCOL

Drug Facts

ACTIVE INGREDIENT

Arbutin, Adenosine

INACTIVE INGREDIENT

Water, Butylene Glycol, etc.

PURPOSE

Skin Protectant

keep out of reach of the children

INDICATIONS AND USAGE

How To Use: Take moderate amount and spread it over desired area for natural skin tone evenly.

It can be used as regenerative cream for irritated skin or after peeling. You can apply it before sleeping due to excellent regenerative effect.

WARNINGS

Precautions

1. If the cosmetic causes red rash, swollenness or itching by exposure to sunlight during the use, you are advised to stop using it immediately and you may consult a pharmacist or a doctor

2. It is not advised to use the cosmetic on the skin where you have scars

3. Precautions for storage

ⓐ Keep it out of infants or children’s reach

ⓑ Keep it out of the place where exposure to direct sunlight exists

DOSAGE AND ADMINISTRATION

for external use only